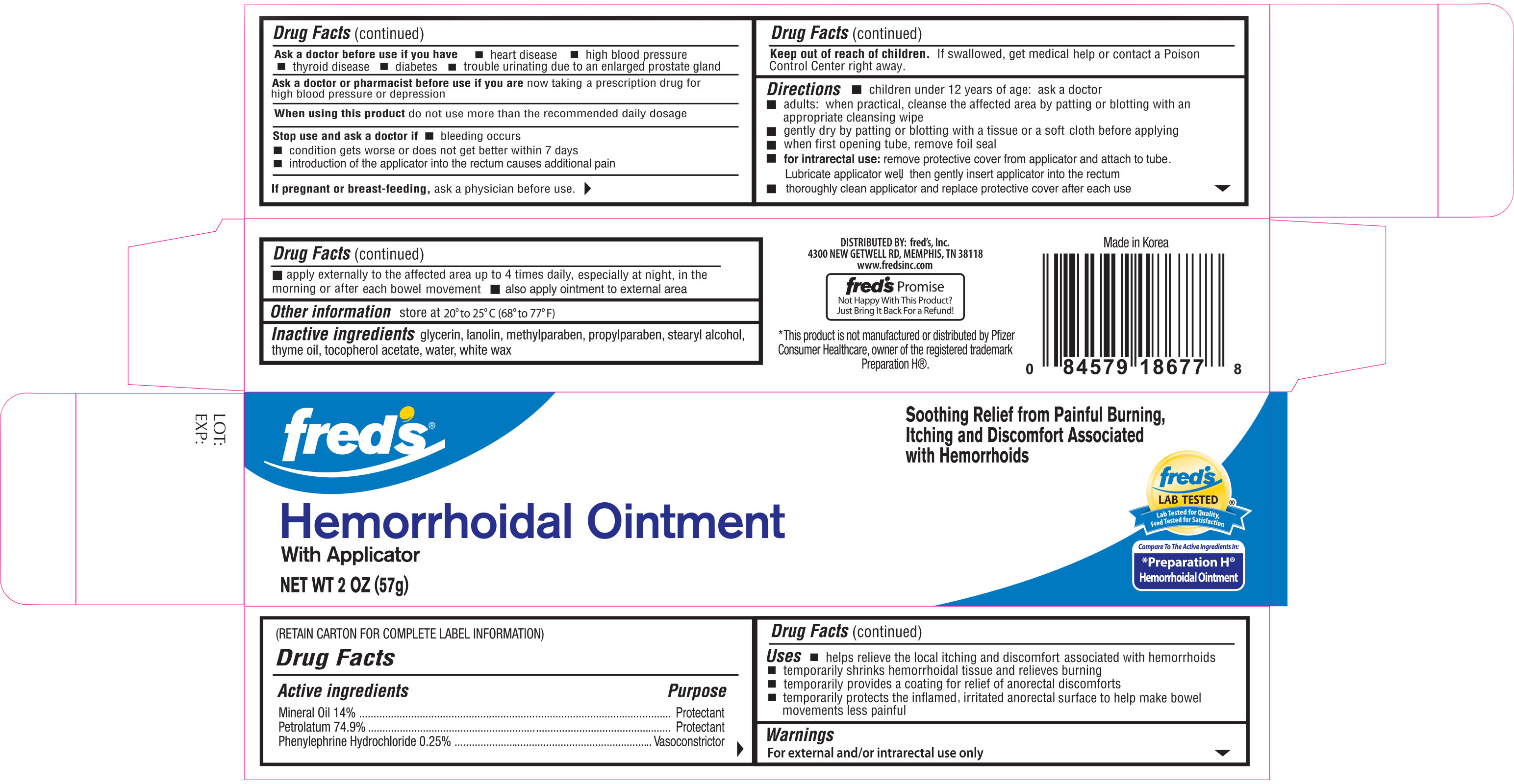 DRUG LABEL: Freds Hemorrhoidal
NDC: 55315-336 | Form: CREAM
Manufacturer: Freds, Inc
Category: otc | Type: HUMAN OTC DRUG LABEL
Date: 20171212

ACTIVE INGREDIENTS: MINERAL OIL 140 mg/1 g; PETROLATUM 749 mg/1 g; PHENYLEPHRINE HYDROCHLORIDE 2.5 mg/1 g
INACTIVE INGREDIENTS: GLYCERIN; LANOLIN; METHYLPARABEN; PROPYLPARABEN; STEARYL ALCOHOL; THYME OIL; ALPHA-TOCOPHEROL ACETATE; WATER; WHITE WAX

Fred's Hemorrhoidal Ointment 2oz w/applicator NBE Preparation H

Active Ingredients Purpose

Mineral Oil 14%................................................... Protectant

Petrolatum 74.9%................................................ Protectant

Phenylephrine Hydrochloride 0.25%........................ Vasoconstrictor

Uses

- Helps relieve the local itching and discomfort associated with hemorrhoids
- Temporarily shrinks hemorrhoidal tissue and relieves burning
- Temporarily provides a coating for relief of anorectal discomforts
- Temporarily protects the inflamed, irritated anorectal surface to help make bowel movements less painful

Warnings

For external and/or intrarectal use only

Ask a doctor before use if you have:

- heart disease
- high blood pressure
- thyroid disease
- diabetes
- trouble urinating due to an enlarged prostate gland

Ask a doctor or pharmacist before use if you are now taking a prescription drug for high blood pressure or depression

Stop use and ask a doctor if:

- bleeding occurs
- condition gets worse or does not get better within 7 days
- introduction of the applicator into the rectum causes additional pain

PREGNANCY OR BREAST FEEDING

If pregnant or breast-feeding, ask a physician before use

Keep out of reach of children. If swallowed, get medical help or contact a Poison Control Center right away.

Directions:

- children under 12 years of age: ask a doctor
- adults: when practical, cleanse the affected area by patting or blotting with an appropriate cleansing wipe
- gently dry by patting or blotting with a tissue or a soft cloth before applying
- when first opening tube, remove foil seal
- for intrarectal use: remove protective cover from applicator and attach to tube. Lubricate applicator well, then gently insert applicator into the rectum
- thoroughly clean applicator and replace protective cover after each use
- apply externally to the affected area up to 4 times daily, especially at night, in the morning, or after each bowel movement
- also apply ointment to external area

Other Information

store at 20° to 25°C (68° to 77°F)

Inactive Ingredients

glycerin, lanolin, methylparaben, proplyparaben, steryl alcohol, thyme oil, tocopherol acetate, water, white wax

DOSAGE AND ADMINISTRATION

DISTRIBUTED BY:

FRED'S, INC.

4300 NEW GETWELL RD.

MEMPHIS, TN 38118 USA